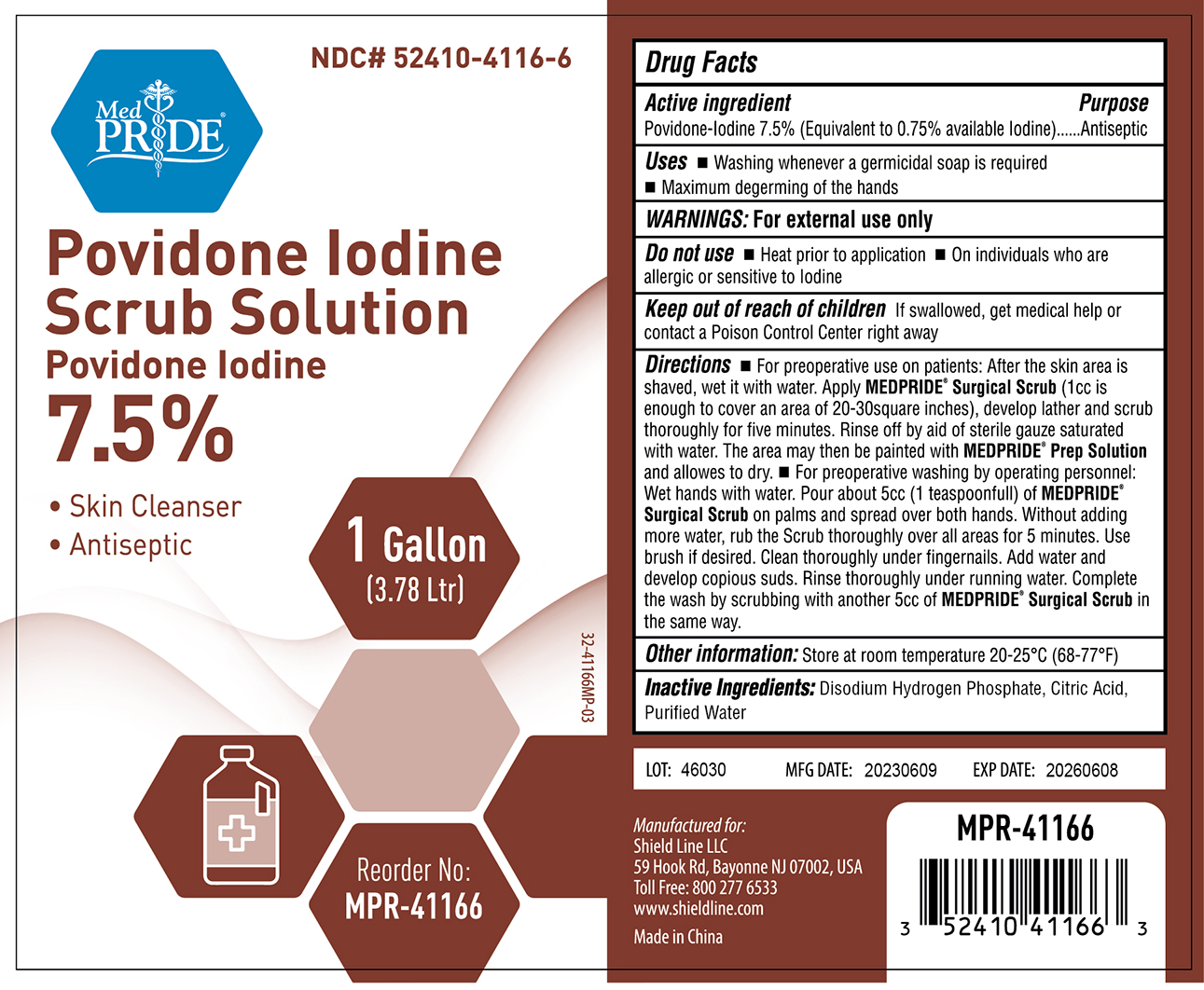 DRUG LABEL: MedPride Povidone Iodine Scrub Solution
NDC: 52410-4116 | Form: SOLUTION
Manufacturer: Shield Line LLC
Category: otc | Type: HUMAN OTC DRUG LABEL
Date: 20250818

ACTIVE INGREDIENTS: POVIDONE-IODINE 75 mg/1 mL
INACTIVE INGREDIENTS: CITRIC ACID ACETATE; SODIUM PHOSPHATE, DIBASIC, ANHYDROUS; WATER

Povidone Iodine Scrub Solution 7.5 %

Active Ingredient

Povidone Iodine, 7.5% (equivalent to .75% available Iodine)

Purpose

Antiseptic

Uses

- Washing whenever a germicidal soap is required
- Maximum degerming of the hands

WARNINGS:

For External Use Only

Keep out of reach of children

- If swallowed, get medical help or contact a Poison Control Center right away

Directions

- Apply necessary quantity Degasa Surgical Scrub on area to wash on patients for preoperative or for operating personnel.
- Distributing thoroughly Degasa Surgical Scrub on the desired area, rubbing at least 5 minutes.
- On patients, rinse off with a sterile gauze saturated with water. On operating personnel, rinse the hands under running water, clean under fingernails use brush if desired.
- On operations personnel complete disinfection with another wash with the same way.

Inactive ingredients

Disodium Hydrogen Phosphate,Citric Acid, Purified Water